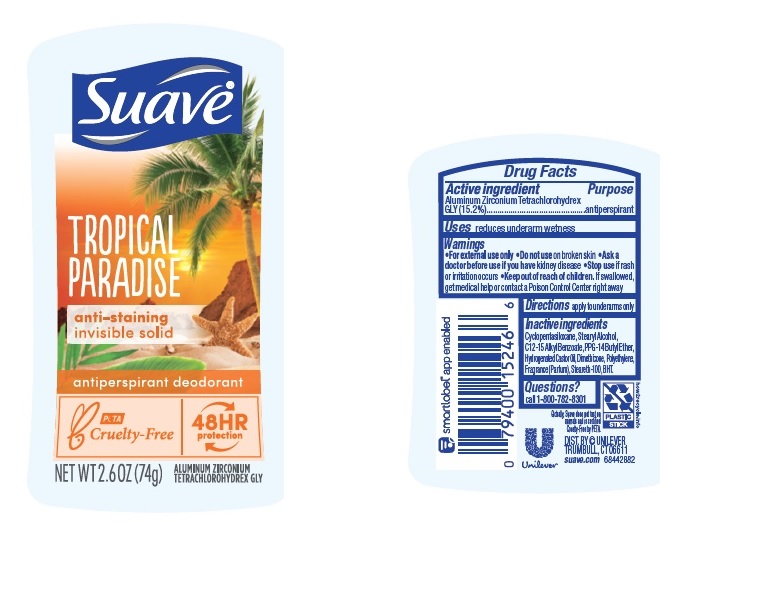 DRUG LABEL: Suave
NDC: 64942-1774 | Form: STICK
Manufacturer: Conopco Inc. d/b/a/ Unilever
Category: otc | Type: HUMAN OTC DRUG LABEL
Date: 20221207

ACTIVE INGREDIENTS: ALUMINUM ZIRCONIUM TETRACHLOROHYDREX GLY 15.2 g/100 g
INACTIVE INGREDIENTS: HIGH DENSITY POLYETHYLENE; STEARETH-100; HYDROGENATED CASTOR OIL; ALKYL (C12-15) BENZOATE; PPG-14 BUTYL ETHER; CYCLOMETHICONE 5; BUTYLATED HYDROXYTOLUENE; STEARYL ALCOHOL; DIMETHICONE

Suave Tropical Paradise 48HR Protection Antiperspirant Deodorant

SUAVE TROPICAL PARADISE 48HR PROTECTION ANTIPERSPIRANT DEODORANT - aluminum zirconium tetrachlorohydrex gly stick

Suave Tropical Paradise 48HR Protection Antiperspirant Deodorant

Drug Facts

Active ingredient

Aluminum Zirconium Tetrachlorohydrex GLY (15.2 %)

Purpose

antiperspirant

Uses

reduces underarm wetness

Warnings

• For externaluse only.
• Do not use on broken skin .
• Ask a doctor before use if you have kidney disease.
• Stop use if rash or irritation occurs.

• Keep out of reach of children.

If swallowed, get medical help or contact a Poison Control Center right away.

Directions

apply to underarms only

Inactive ingredients

Cyclopentasiloxane, Stearyl Alcohol, C12-15 Alkyl Benzoate, PPG-14 Butyl Ether, Hydrogenated Castor Oil, Dimethicone, Polyethylene, Fragrance (Parfum), Steareth-100, BHT.